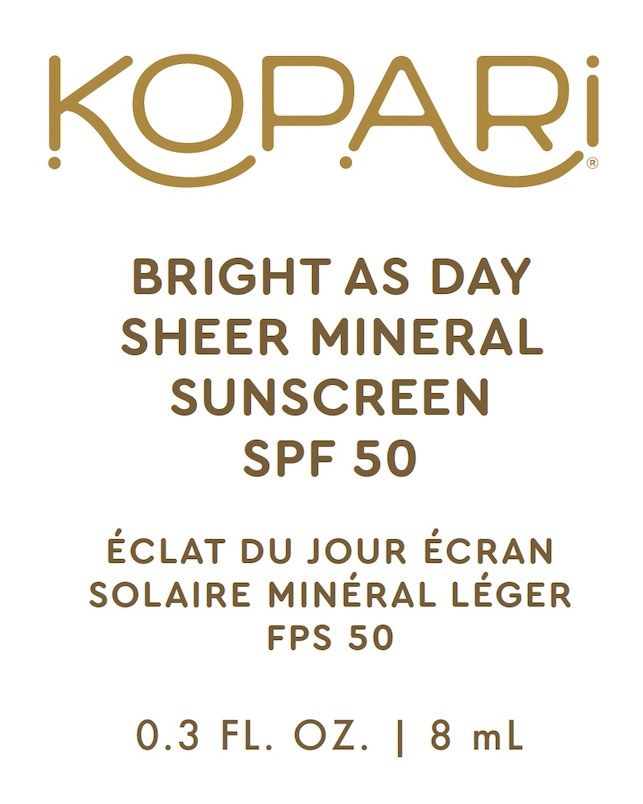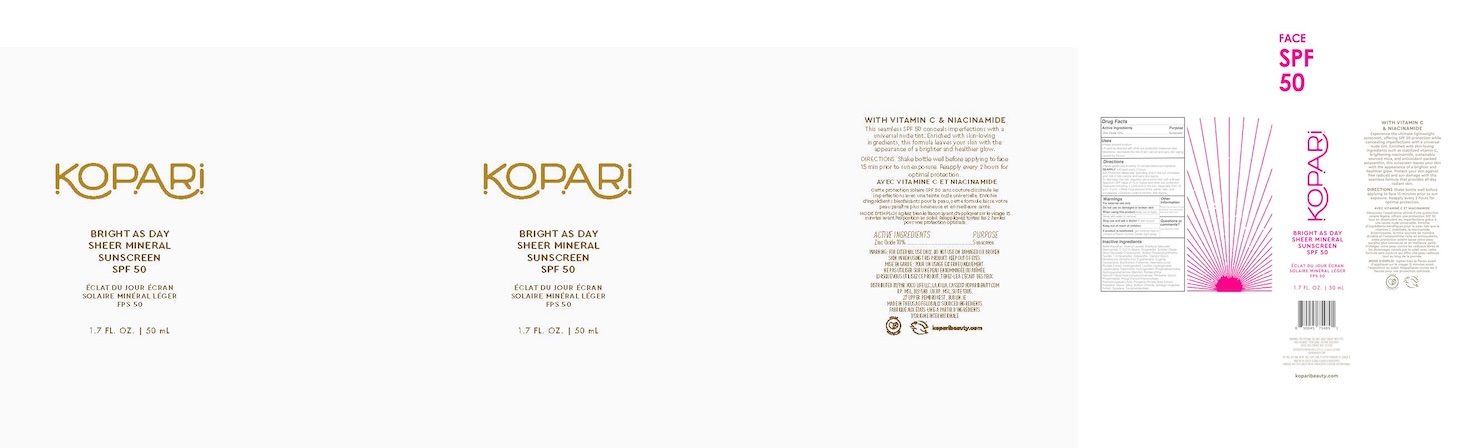 DRUG LABEL: Bright as Day Mineral SPF50
NDC: 84130-005 | Form: CREAM
Manufacturer: Koco Life LLC
Category: otc | Type: HUMAN OTC DRUG LABEL
Date: 20240923

ACTIVE INGREDIENTS: ZINC OXIDE 100 mg/1 mL
INACTIVE INGREDIENTS: LAURYL GLUCOSIDE; POLYGLYCERYL-6 LAURATE; ETHYL FERULATE; FERRIC OXIDE YELLOW; POLYGLYCERYL-6 POLYRICINOLEATE; MYRISTYL GLUCOSIDE; CLOVE; 1,2-HEXANEDIOL; HAEMATOCOCCUS PLUVIALIS; SODIUM POLYACRYLOYLDIMETHYL TAURATE; ERGOTHIONEINE; FERROSOFERRIC OXIDE; FERRIC OXIDE RED; WATER; MICA; POLYHYDROXYSTEARIC ACID (2300 MW); PHENYL TRIMETHICONE; AMINOPROPYL ASCORBYL PHOSPHATE; BUTYLOCTYL SALICYLATE; SOLIDAGO VIRGAUREA WHOLE; HYDROXYACETOPHENONE; DISTEARDIMONIUM HECTORITE; SILICON DIOXIDE; .ALPHA.-TOCOPHEROL ACETATE; ISOAMYL LAURATE; C13-15 ALKANE; NIACINAMIDE; ASTAXANTHIN; PONGAMOL; HYDROGENATED SOYBEAN LECITHIN; TITANIUM DIOXIDE; MANNITOL; ISOPROPYL TITANIUM TRIISOSTEARATE; CAPRYLYL GLYCOL; PROPANEDIOL

Bright as Day Mineral SPF50

Active ingredients

Zinc Oxide 10%

Purpose

Zinc Oxide 10%............Sunscreen

Uses

• Helps prevent sunburn

• If used as directed with other sun protection measures (see Directions), decreases the risk of skin cancer and early skin aging caused by the sun

Warnings

For external use only

Do not use on damaged or broken skin

When using this product keep out of eyes. Rinse with water to remove

Stop use and ask a doctor if rash occurs

Keep out of reach of children

If product is swallowed, get medical help or contact a Poison Control Center right away

Directions

• Apply generously & evenly 15 minutes before sun exposure.

REAPPLY: • At least every 2 hours

Sun Protection Measures: spending time in the sun increases your risk of skin cancer and early skin aging.To decrease this risk, regularly use a sunscreen with a Broad Spectrum SPF value of 15 or higher and other sun protection measures including: • Limit time in the sun, especially from 10 a.m.- 2 p.m. • Wear long-sleeved shirts, pants, hats, and sunglasses. • Children under 6 months: Ask doctor

Inactive ingredients

Water/Aqua/Eau, Isoamyl Laurate, Propanediol, Butyloctyl Salicylate, C13-15 Alkane, Niacinamide, Mica, Sodium Polyacryloyldimethyl Taurate, Lauryl Glucoside, Polyhydroxystearic Acid, Polyglyceryl-6 Laurate, Silica, Ethyl Ferulate, Hydrogenated Lecithin, Titanium Dioxide (CI 77891), Polyglyceryl-6 Polyricinoleate, Tocopheryl Acetate, Hydroxyacetophenone, Phenyl Trimethicone, Myristyl Glucoside, Iron Oxides (CI 77492), Pongamol, Caprylyl Glycol, Eugenia Caryophyllus (Clove) Bud Extract, Solidago Virgaurea (Goldenrod) Extract, Aminopropyl Ascorbyl Phosphate, Mannitol, 1,2-Hexanediol, Disteardimonium Hectorite, Iron Oxides (Ci 77491), Iron Oxides (Ci 77499), Isopropyl Titanium Triisostearate, Haematococcus Pluvialis Extract, Ergothioneine, Astaxanthin.

Other information

Protect the product in this container from excessive heat and direct sun

Questions or comments?

Call (858) 252-0099

PACKAGE LABEL

Kopari

Bright as Day

Sheer Mineral

Sunscreen

SPF 50

1.7 FL. OZ. | 50 mL